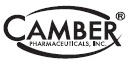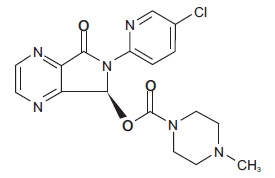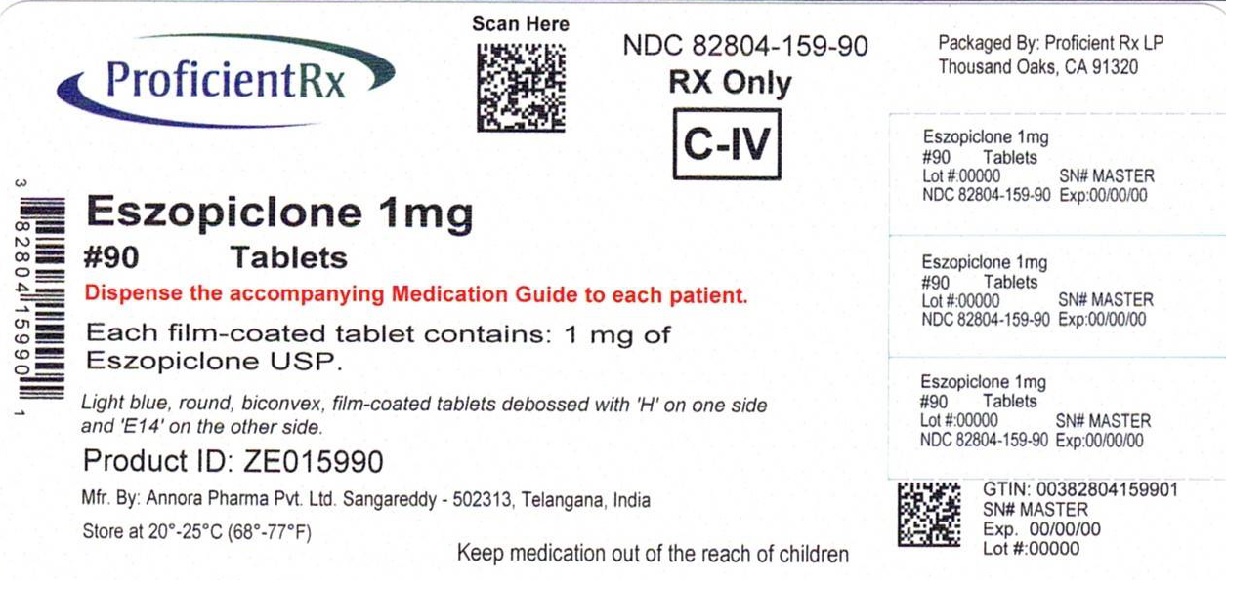 DRUG LABEL: Eszopiclone
NDC: 82804-159 | Form: TABLET, FILM COATED
Manufacturer: Proficient Rx LP
Category: prescription | Type: HUMAN PRESCRIPTION DRUG LABEL
Date: 20260201
DEA Schedule: CIV

ACTIVE INGREDIENTS: ESZOPICLONE 1 mg/1 1
INACTIVE INGREDIENTS: ANHYDROUS DIBASIC CALCIUM PHOSPHATE; CROSCARMELLOSE SODIUM; SILICON DIOXIDE; HYPROMELLOSE 2910 (6 MPA.S); LACTOSE MONOHYDRATE; MAGNESIUM STEARATE; MICROCRYSTALLINE CELLULOSE 102; POLYETHYLENE GLYCOL 3350; TITANIUM DIOXIDE; TRIACETIN; FD&C BLUE NO. 2

HIGHLIGHTS OF PRESCRIBING INFORMATION

These highlights do not include all the information needed to use ESZOPICLONE TABLETS safely and effectively. See full prescribing information for ESZOPICLONE TABLETS.
ESZOPICLONE tablets, for oral use, CIV
Initial U.S. Approval: 2004

RECENT MAJOR CHANGES

Boxed Warning 08/2019
Contraindications (Error! Hyperlink reference not valid.) 08/2019
Warnings and Precautions, Complex Sleep Behaviors (Error! Hyperlink reference not valid.) 08/2019
Warnings and Precautions, CNS Depressant Effects and Next-Day Impairment (Error! Hyperlink reference not valid.) 12/2018

1 INDICATIONS & USAGE

Eszopiclone tablets are indicated for the treatment of insomnia. Eszopiclone tablets has been shown to decrease sleep latency and improve sleep maintenance (Error! Hyperlink reference not valid.)

2 DOSAGE & ADMINISTRATION

• Use the lowest dose effective for the patient ()
• Recommended initial dose is 1 mg, immediately before bedtime, with at least 7 to 8 hours remaining before the planned time of awakening. May increase dose if clinically indicated, to a maximum of 3 mg (Error! Hyperlink reference not valid.)
• Geriatric or debilitated patients: Dose should not exceed 2 mg (Error! Hyperlink reference not valid.)
• Patients with severe hepatic impairment, or taking potent CYP3A4 inhibitors: Dose should not exceed 2 mg (Error! Hyperlink reference not valid.)
• Do not take with or immediately after a meal (Error! Hyperlink reference not valid.)

3 DOSAGE FORMS & STRENGTHS

Tablets: 1 mg, 2 mg, and 3 mg (Error! Hyperlink reference not valid.)

4 CONTRAINDICATIONS

• Patients who have experienced complex sleep behaviors after taking eszopiclone tablets (Error! Hyperlink reference not valid.)
• Known hypersensitivity to eszopiclone (Error! Hyperlink reference not valid.)

5 WARNINGS AND PRECAUTIONS

• CNS Depressant Effects Impaired alertness and motor coordination, including risk of morning impairment. Risk increases with dose and use with other CNS depressants and alcohol. Caution patients taking 3 mg dose against driving and against activities requiring complete mental alertness during the morning after use. (Error! Hyperlink reference not valid.)
• Evaluate for Comborbid DiagnosesReevaluate if insomnia persists after 7 to 10 days of use (Error! Hyperlink reference not valid.)
• Severe Anaphylactic/Anaphylactoid Reactions(angioedema and anaphylaxis have been reported): Do not rechallenge if such reactions occur (Error! Hyperlink reference not valid.)
• Abnormal Thinking amd Behavioral Changes including decreased inhibition, bizarre behavior, agitation and depersonalization have been reported. Immediately evaluate any new onset of behavioral changes (Error! Hyperlink reference not valid.)
• Worsening of Depression or Suicidal Thinkingmay occur: Prescribe the least number of tablets feasible to avoid intentional overdose (Error! Hyperlink reference not valid., Error! Hyperlink reference not valid.)
• Withdrawal EffectsSymptoms may occur with rapid dose reduction or discontinuation (Error! Hyperlink reference not valid., Error! Hyperlink reference not valid.)
• Elderly PatientsUse lower dose due to impaired motor, cognitive performance and increased sensitivity (Error! Hyperlink reference not valid., Error! Hyperlink reference not valid.)
• Patients with Hepatic Impairment, Impaired Respiratory Function, Impaired Drug Metabolism or Hemodynamic ResponsesUse with caution (Error! Hyperlink reference not valid.)

6 ADVERSE REACTIONS

Most commonly observed adverse reactions (incidence ≥2%) were unpleasant taste, headache, somnolence, respiratory infection, dizziness, dry mouth, rash, anxiety, hallucinations, and viral infections (Error! Hyperlink reference not valid.)

To report SUSPECTED ADVERSE REACTIONS, contact Annora Pharma Private Limited at 1-866-495-1995 or FDA at 1-800-FDA-1088 or ww.fda.gov/medwatch.

7 DRUG INTERACTIONS

• CNS DepressantsAdditive CNS-depressant effects with combination use. Use with ethanol causes additive psychomotor impairment (Error! Hyperlink reference not valid.)
• RifampicinCombination use may decrease exposure and effects of eszopiclone tablets (Error! Hyperlink reference not valid.)
• KetoconazoleCombination use increases exposure and effect of eszopiclone tablets. Dose reduction of eszopiclone tablet is needed (Error! Hyperlink reference not valid.)

8 USE IN SPECIFIC POPULATIONS

• Pediatric UseSafety and effectiveness not established. Dizziness, dysgeusia, hallucinations, suicidal ideation reported (Error! Hyperlink reference not valid.)

FULL PRESCRIBING INFORMATION

1 INDICATIONS & USAGE

Eszopiclone tablets are indicated for the treatment of insomnia. In controlled outpatient and sleep laboratory studies, eszopiclone tablets administered at bedtime decreased sleep latency and improved sleep maintenance.
The clinical trials performed in support of efficacy were up to 6 months in duration. The final formal assessments of sleep latency and maintenance were performed at 4 weeks in the 6-week study (adults only), at the end of both 2-week studies (elderly only) and at the end of the 6-month study (adults only).

2 DOSAGE & ADMINISTRATION

Use the lowest effective dose for the patient.

2.1 Dosage in Adults

The recommended starting dose is 1 mg. Dosing can be raised to 2 mg or 3 mg if clinically indicated. In some patients, the higher morning blood levels of eszopiclone tablets following use of the 2 mg or 3 mg dose increase the risk of next day impairment of driving and other activities that require full alertness [ see Error! Hyperlink reference not valid.]. The total dose of eszopiclone tablets should not exceed 3 mg, once daily immediately before bedtime [ see Error! Hyperlink reference not valid.].

2.2 Geriatric or Debilitated Patients

The total dose of eszopiclone tablets should not exceed 2 mg in elderly or debilitated patients.

2.3 Patients with Severe Hepatic Impairment, or Taking Potent CYP3A4 Inhibitors

In patients with severe hepatic impairment, or in patients coadministered eszopiclone tablets with potent CYP3A4 inhibitors, the total dose of eszopiclone tablets should not exceed 2 mg [ see Error! Hyperlink reference not valid.].

2.4 Use with CNS Depressants

Dosage adjustments may be necessary when eszopiclone tablets are combined with othercentral nervous system (CNS) depressant drugs because of the potentially additive effects [ see Error! Hyperlink reference not valid.].

2.5 Administration with Food

Taking eszopiclone tablets with or immediately after a heavy, high-fat meal results in slower absorption and would be expected to reduce the effect of eszopiclone tablets on sleep latency [see Error! Hyperlink reference not valid.].

3 DOSAGE FORMS & STRENGTHS

Eszopiclone tablets, USP are available in 1 mg, 2 mg and 3 mg strengths for oral administration.
Eszopiclone tablets USP, 3 mg are dark blue to blue, round, biconvex, film-coated tablets debossed with ‘H’ on one side and ‘E16’ on the other side.
Eszopiclone tablets USP, 2 mg are white to off-white, round, biconvex, film-coated tablets debossed with ‘H’ on one side and ‘E15’ on the other side.
Eszopiclone tablets USP, 1 mg are light blue, round, biconvex, film-coated tablets debossed with ‘H’ on one side and ‘E14’ on the other side.

4 CONTRAINDICATIONS

• Eszopiclonetablet is contraindicated in patients who have experienced complex sleep behaviors after taking eszopiclone tablets [see Error! Hyperlink reference not valid.].
• Eszopiclone tablet is contraindicated in patients with known hypersensitivity to eszopiclone. Hypersensitivity reactions include anaphylaxis and angioedema [see Error! Hyperlink reference not valid.].

5 WARNINGS AND PRECAUTIONS

5.1 Complex Sleep Behaviours

Complex sleepbehaviors including sleep-walking, sleep-driving, and engaging in other activities while not fully awake may occur following the first or any subsequent use of eszopiclone tablet. Patients can be seriously injured or injure others during complex sleep behaviors. Such injuries may result in a fatal outcome. Other complex sleep behaviors (e.g., preparing and eating food, making phone calls, or having sex) have also been reported. Patients usually do not remember these events. Post-marketing reports have shown that complex sleep behaviors may occur with eszopiclone alone at recommended dosages, with or without the concomitant use of alcohol or other CNS depressants [see Error! Hyperlink reference not valid.]. Discontinue eszopiclone immediately if a patient experiences a complex sleep behavior.

5.2 CNS Depressant Effects and Next-Day Impairment

Eszopiclone tablet is a CNS depressant and can impair daytime function in some patients at the higher doses (2 mg or 3 mg), even when used as prescribed. Prescribers should monitor for excess depressant effects, but impairment can occur in the absence of symptoms (or even with subjective improvement), and impairment may not be reliably detected by ordinary clinical exam (i.e., less than formal psychomotor testing). While pharmacodynamic tolerance or adaptation to some adverse depressant effects of eszopiclone tablets may develop, patients using 3 mg eszopiclone tablets should be cautioned against driving or engaging in other hazardous activities or activities requiring complete mental alertness the day after use.
Additive effects occur with concomitant use of other CNS depressants (e.g., benzodiazepines, opioids, tricyclic antidepressants, alcohol), including daytime use. Downward dose adjustment of eszopiclone tablets and concomitant CNS depressants should be considered [see Error! Hyperlink reference not valid.].
The use of eszopiclone tablets with other sedative-hypnotics at bedtime or the middle of the night is not recommended.
The risk of next-day psychomotor impairment is increased if eszopiclone tablets are taken with less than a full night of sleep remaining (7- to 8 hours); if higher than the recommended dose is taken; if co-administered with other CNS depressants; or coadministered with other drugs that increase the blood levels of eszopiclone [see Error! Hyperlink reference not valid. and Error! Hyperlink reference not valid.].
Becauseeszopiclone tablets can cause drowsiness and a decreased level of consciousness, patients, particularly the elderly, are at higher risk of falls.

5.3 Need to Evaluate for Comborbid Diagnoses

Because sleep disturbances may be the presenting manifestation of a physical and/or psychiatric disorder, symptomatic treatment of insomnia should be initiated only after a careful evaluation of the patient. The failure of insomnia to remit after 7 to 10 days of treatment may indicate the presence of a primary psychiatric and/or medical illness that should be evaluated.Worsening of insomnia or the emergence of new thinking or behavior abnormalities may be the consequence of an unrecognized psychiatric or physical disorder. Such findings have emerged during the course of treatment with sedative/hypnotic drugs, including eszopiclone tablets. Because some of the important adverse effects of eszopiclone tablets appear to be dose related, it is important to use the lowest possible effective dose, especially in the elderly [see Error! Hyperlink reference not valid.].

5.4 Severe Anaphylactic and Anaphylactoid Reactions

Rare cases of angioedema involving the tongue, glottis or larynx have been reported in patients after taking the first or subsequent doses of sedative-hypnotics, including eszopiclone tablets. Some patients have had additional symptoms such as dyspnea, throat closing, or nausea and vomiting that suggest anaphylaxis. Some patients have required medical therapy in the emergency department. If angioedema involves the tongue, glottis or larynx, airway obstruction may occur and be fatal. Patients who develop angioedema after treatment with eszopiclone tablets should not be rechallenged with the drug.

5.5 Abnormal Thinking and Behavioral Changes

A variety of abnormal thinking and behavior changes have been reported to occur in association with the use of sedative/hypnotics. Some of these changes may be characterized by decreased inhibition (e.g., aggressiveness and extroversion that seem out of character), similar to effects produced by alcohol and other CNS depressants. Other reported behavioral changes have included bizarre behavior, agitation, hallucinations, and depersonalization. Amnesia and other neuropsychiatric symptoms may occur unpredictably.
It can rarely be determined with certainty whether a particular instance of the abnormal behaviors listed above is drug induced, spontaneous in origin, or a result of an underlying psychiatric or physical disorder. Nonetheless, the emergence of any new behavioral sign or symptom of concern requires careful and immediate evaluation.

5.6 Withdrawal Effects

Following rapid dose decrease or abrupt discontinuation of the use of sedative/hypnotics, there have been reports of signs and symptoms similar to those associated with withdrawal from other CNS-depressant drugs [see ].

5.7 Timing of Drug Administration

Eszopiclone tablets should be taken immediately before bedtime. Taking a sedative/hypnotic while still up and about may result in short-term memory impairment, hallucinations, impaired coordination, dizziness, and lightheadedness.

5.8 Special Populations

Use in Elderly and/or Debilitated Patients
Impaired motor and/or cognitive performance after repeated exposure or unusual sensitivity to sedative/hypnotic drugs is a concern in the treatment of elderly and/or debilitated patients. The dose should not exceed 2 mg in elderly or debilitated patients [see Error! Hyperlink reference not valid.].
Use in Patients with Concomitant Illness
Clinical experience with eszopiclone in patients with concomitant illness is limited. Eszopiclone tablets should be used with caution in patients with diseases or conditions that could affect metabolism or hemodynamic responses.
A study in healthy volunteers did not reveal respiratory-depressant effects at doses 2.5-fold higher (7 mg) than the recommended dose of eszopiclone. Caution is advised, however, if eszopiclone tablets are prescribed to patients with compromised respiratory function.
The dose of eszopiclone tablets should not exceed 2 mg in patients with severe hepatic impairment, because systemic exposure is doubled in such subjects. No dose adjustment appears necessary for subjects with mild or moderate hepatic impairment. No dose adjustment appears necessary in subjects with any degree of renal impairment, since less than 10% of eszopiclone is excreted unchanged in the urine.
The dose of eszopiclone tablets should be reduced in patients who are administered potent inhibitors of CYP3A4, such as ketoconazole, while taking eszopiclone tablets. Downward dose adjustment is also recommended when eszopiclone tablets are administered with agents having known CNS-depressant effects.
Use in Patients with Depression
In primarily depressed patients treated with sedative-hypnotics, worsening of depression, including suicidal thoughts and actions (including completed suicides), have been reported in association with the use of sedative/hypnotics.
Sedative/hypnotic drugs should be administered with caution to patients exhibiting signs and symptoms of depression. Suicidal tendencies may be present in such patients, and protective measures may be required. Intentional overdose is more common in this group of patients; therefore, the least amount of drug that is feasible should be prescribed for the patient at any one time.

6 ADVERSE REACTIONS

The following are described in more detail in the section of the label:
• Complex Sleep Behaviors [see Boxed Warning and Error! Hyperlink reference not valid.]
• CNS Depressant Effects and Next-Day Impairment [see Error! Hyperlink reference not valid.]
• Need to Evaluate for Comorbid Diagnoses [see Error! Hyperlink reference not valid.]
• Severe Anaphylactic and Anaphylactoid Reactions [see Error! Hyperlink reference not valid.]
• Abnormal Thinking and Behavioral Changes [see Error! Hyperlink reference not valid.]
• Withdrawal Effects [see Error! Hyperlink reference not valid.]
• Timing of Drug Administration [see Error! Hyperlink reference not valid.]
• Special Populations [see Error! Hyperlink reference not valid.]
Because clinical trials are conducted under widely varying conditions, adverse reaction rates observed in the clinical trials of a drug cannot be directly compared to rates in the clinical trials of another drug and may not reflect the rates observed in clinical practice.
The premarketing development program for eszopiclone tablets included eszopiclone exposures in patients and/or normal subjects from two different groups of studies: approximately 400 normal subjects in clinical pharmacology/pharmacokinetic studies, and approximately 1550 patients in placebo-controlled clinical effectiveness studies, corresponding to approximately 263 patient-exposure years. The conditions and duration of treatment with eszopiclone tablets varied greatly and included (in overlapping categories) open-label and double-blind phases of studies, inpatients and outpatients, and short-term and longer-term exposure. Adverse reactions were assessed by collecting adverse events, results of physical examinations, vital signs, weights, laboratory analyses, and ECGs.
The stated frequencies of adverse reactions represent the proportion of individuals who experienced, at least once, adverse reaction of the type listed. A reaction was considered treatment-emergent if it occurred for the first time or worsened while the patient was receiving therapy following baseline evaluation.

6.1 Clinical Trials Experience

Adverse Reactions Resulting in Discontinuation of Treatment
In placebo-controlled, parallel-group clinical trials in the elderly, 3.8% of 208 patients who received placebo, 2.3% of 215 patients who received 2 mg eszopiclone tablets, and 1.4% of 72 patients who received 1 mg eszopiclone tablets discontinued treatment due to an adverse reaction. In the 6-week parallel-group study in adults, no patients in the 3 mg arm discontinued because of an adverse reaction. In the long-term 6-month study in adult insomnia patients, 7.2% of 195 patients who received placebo and 12.8% of 593 patients who received 3 mg eszopiclone tablets discontinued due to an adverse reaction. No reaction that resulted in discontinuation occurred at a rate of greater than 2%.
Adverse Reactions Observed at an Incidence of ≥2% in Controlled Trials
Table 1 shows the incidence of adverse reactions from a Phase 3 placebo-controlled study of eszopiclone tablets at doses of 2 or 3 mg in nonelderly adults. Treatment duration in this trial was 44 days. The table includes only reactions that occurred in 2% or more of patients treated with eszopiclone tablets 2 mg or 3 mg in which the incidence in patients treated with eszopiclone was greater than the incidence in placebo-treated patients.
Table 1: Incidence (%) of Adverse Reactions in a 6-Week Placebo-Controlled Study in Nonelderly Adults with Eszopiclone Tablets ^1

Adverse Reaction | Placebo (n=99) | Eszopiclone tablets 2 mg (n=104) | Eszopiclone tablets 3 mg (n=105)
Body as a Whole
Headache | 13 | 21 | 17
Viral Infection | 1 | 3 | 3
Digestive System
Dry Mouth | 3 | 5 | 7
Dyspepsia | 4 | 4 | 5
Nausea | 4 | 5 | 4
Vomiting | 1 | 3 | 0
Nervous System
Anxiety | 0 | 3 | 1
Confusion | 0 | 0 | 3
Depression | 0 | 4 | 1
Dizziness | 4 | 5 | 7
Hallucinations | 0 | 1 | 3
Libido Decreased | 0 | 0 | 3
Nervousness | 3 | 5 | 0
Somnolence | 3 | 10 | 8
Respiratory System
Infection | 3 | 5 | 10
Skin and Appendages
Rash | 1 | 3 | 4
Special Senses
Unpleasant Taste | 3 | 17 | 34
Urogenital System
Dysmenorrhea * | 0 | 3 | 0
Gynecomastia ** | 0 | 3 | 0

^1Reactions for which the eszopiclone tablets incidence was equal to or less than placebo are not listed on the table, but included the following: abnormal dreams, accidental injury, back pain, diarrhea, flu syndrome, myalgia, pain, pharyngitis, and rhinitis.

* Gender-specific adverse reaction in females
** Gender-specific adverse reaction in males
Adverse reactions from Table 1 that suggest a dose-response relationship in adults include viral infection, dry mouth, dizziness, hallucinations, infection, rash, and unpleasant taste, with this relationship clearest for unpleasant taste.
Table 2 shows the incidence of adverse reactions from combined Phase 3 placebo-controlled studies of eszopiclone tablets at doses of 1 or 2 mg in elderly adults (ages 65 to 86). Treatment duration in these trials was 14 days. The table includes only reactions that occurred in 2% or more of patients treated with eszopiclone tablets 1 mg or 2 mg in which the incidence in patients treated with eszopiclone tablets was greater than the incidence in placebo-treated patients.
Table 2: Incidence (%) of Adverse Reactions in Elderly Adults (Ages 65 to 86 Years) in 2-Week Placebo-Controlled Trials with Eszopiclone Tablets 1

Adverse Reactions | Placebo (n=208) | Eszopiclone tablets 1 mg (n=72) | Eszopiclone tablets 2 mg (n=215)
Body as a Whole
Accidental Injury | 1 | 0 | 3
Headache | 14 | 15 | 13
Pain | 2 | 4 | 5
Digestive System
Diarrhea | 2 | 4 | 2
Dry Mouth | 2 | 3 | 7
Dyspepsia | 2 | 6 | 2
Nervous System
Abnormal Dreams | 0 | 3 | 1
Dizziness | 2 | 1 | 6
Nervousness | 1 | 0 | 2
Neuralgia | 0 | 3 | 0
Skin and Appendages
Pruritus | 1 | 4 | 1
Special Senses
Unpleasant Taste | 0 | 8 | 12
Urogenital System
Urinary Tract Infection | 0 | 3 | 0

1 Reactions for which the eszopiclone tablets incidence was equal to or less than placebo are not listed on the table, but included the following: abdominal pain, asthenia, nausea, rash, and somnolence.

Adverse reactions from Table 2 that suggest a dose-response relationship in elderly adults include pain, dry mouth, and unpleasant taste, with this relationship again clearest for unpleasant taste.
These figures cannot be used to predict the incidence of adverse reactions in the course of usual medical practice because patient characteristics and other factors may differ from those that prevailed in the clinical trials. Similarly, the cited frequencies cannot be compared with figures obtained from other clinical investigations involving different treatments, uses, and investigators. The cited figures, however, do provide the prescribing physician with some basis for estimating the relative contributions of drug and nondrug factors to the adverse reaction incidence rate in the population studied.
Other Reactions Observed During the Premarketing Evaluation of Eszopiclone Tablets
Following is a list of modified COSTART terms that reflect adverse reactions as defined in the introduction to the Adverse Reactionssection and reported by approximately 1550 subjects treated with eszopiclone tablets at doses in the range of 1 to 3.5 mg/day during Phase 2 and 3 clinical trials throughout the United States and Canada. All reported reactions are included except those already listed in Tables 1 and 2 or elsewhere in labeling, minor reactions common in the general population, and reactions unlikely to be drug-related. Although the reactions reported occurred during treatment with eszopiclone tablets, they were not necessarily caused by it.
Reactions are further categorized by body system and listed in order of decreasing frequency according to the following definitions: frequentadverse reactions are those that occurred on one or more occasions in at least 1/100 patients; infrequentadverse reactions are those that occurred in fewer than 1/100 patients but in at least 1/1,000 patients; rareadverse reactions are those that occurred in fewer than 1/1,000 patients. Gender-specific reactions are categorized based on their incidence for the appropriate gender.
Body as a Whole: Frequent:chest pain; Infrequent:allergic reaction, cellulitis, face edema, fever, halitosis, heat stroke, hernia, malaise, neck rigidity, photosensitivity.
Cardiovascular System: Frequent:migraine; Infrequent:hypertension; Rare:thrombophlebitis.
Digestive System: Infrequent:anorexia, cholelithiasis, increased appetite, melena, mouth ulceration, thirst, ulcerative stomatitis; Rare:colitis, dysphagia, gastritis, hepatitis, hepatomegaly, liver damage, stomach ulcer, stomatitis, tongue edema, rectal hemorrhage.
Hemic and Lymphatic System: Infrequent:anemia, lymphadenopathy.
Metabolic and Nutritional: Frequent:peripheral edema; Infrequent:hypercholesteremia, weight gain, weight loss; Rare:dehydration, gout, hyperlipemia, hypokalemia.
Musculoskeletal System: Infrequent:arthritis, bursitis, joint disorder (mainly swelling, stiffness, and pain), leg cramps, myasthenia, twitching; Rare:arthrosis, myopathy, ptosis.
Nervous System: Infrequent:agitation, apathy, ataxia, emotional lability, hostility, hypertonia, hypesthesia, incoordination, insomnia, memory impairment, neurosis, nystagmus, paresthesia, reflexes decreased, thinking abnormal (mainly difficulty concentrating), vertigo; Rare:abnormal gait, euphoria, hyperesthesia, hypokinesia, neuritis, neuropathy, stupor, tremor.
Respiratory System: Infrequent:asthma, bronchitis, dyspnea, epistaxis, hiccup, laryngitis.
Skin and Appendages: Infrequent:acne, alopecia, contact dermatitis, dry skin, eczema, skin discoloration, sweating, urticaria; Rare:erythema multiforme, furunculosis, herpes zoster, hirsutism, maculopapular rash, vesiculobullous rash.
Special Senses: Infrequent:conjunctivitis, dry eyes, ear pain, otitis externa, otitis media, tinnitus, vestibular disorder; Rare:hyperacusis, iritis, mydriasis, photophobia.
Urogenital System: Infrequent:amenorrhea, breast engorgement, breast enlargement, breast neoplasm, breast pain, cystitis, dysuria, female lactation, hematuria, kidney calculus, kidney pain, mastitis, menorrhagia, metrorrhagia, urinary frequency, urinary incontinence, uterine hemorrhage, vaginal hemorrhage, vaginitis; Rare:oliguria, pyelonephritis, urethritis.

6.2 Postmarketing Experience

In addition to the adverse reactions observed during clinical trials, dysosmia, an olfactory dysfunction that is characterized by distortion of the sense of smell, has been reported during postmarketing surveillance with eszopiclone tablets. Because this event is reported spontaneously from a population of unknown size, it is not possible to estimate the frequency of this event.

7 DRUG INTERACTIONS

7.1 CNS Active Drugs

Ethanol:An additive effect on psychomotor performance was seen with coadministration of eszopiclone and ethanol [see Error! Hyperlink reference not valid., Error! Hyperlink reference not valid.].
Olanzapine:Coadministration of eszopiclone and olanzapine produced a decrease in DSST scores. The interaction was pharmacodynamic; there was no alteration in the pharmacokinetics of either drug.

7.2 Drugs that Inhibit or Induce CYP3A4

Drugs that Inhibit CYP3A4 (Ketoconazole)
CYP3A4 is a major metabolic pathway for elimination of eszopiclone. The exposure of eszopiclone was increased by coadministration of ketoconazole, a potent inhibitor of CYP3A4. Other strong inhibitors of CYP3A4 (e.g., itraconazole, clarithromycin, nefazodone, troleandomycin, ritonavir, nelfinavir) would be expected to behave similarly. Dose reduction of eszopiclone tablet is needed for patient co-administered eszopiclone tablets with potent CYP3A4 inhibitors [see Error! Hyperlink reference not valid.] .
Drugs that Induce CYP3A4 (Rifampicin)
Racemic zopiclone exposure was decreased 80% by concomitant use of rifampicin, a potent inducer of CYP3A4. A similar effect would be expected with eszopiclone. Combination use with CYP3A4 inducer may decrease the exposure and effects of eszopiclone tablets.

8 USE IN SPECIFIC POPULATIONS

8.1 Pregnancy

Risk Summary
Available pharmacovigilance data with eszopiclone use in pregnant women are insufficient to identify a drug-associated risk of major birth defects, miscarriage, or adverse maternal or fetal outcomes. In animal reproduction studies conducted in pregnant rats and rabbits throughout organogenesis, there was no evidence of teratogenicity. Administration of eszopiclone to rats throughout pregnancy and lactation resulted in offspring toxicities at all doses tested; the lowest dose was approximately 200 times the maximum recommended human dose (MRHD) of 3 mg/day based on mg/m ^2body surface area (See Data).
The estimated background risk of major birth defects and miscarriage for the indicated population is unknown. All pregnancies have a background risk of birth defect, loss, or other adverse outcomes. In the U.S. general population, the estimated background risk of major birth defects and miscarriage in clinically recognized pregnancies is 2 to 4% and 15 to 20%, respectively.
Data
Animal Data
Oral administration of eszopiclone to pregnant rats (62.5, 125, or 250 mg/kg/day) and rabbits (4, 8, or 16 mg/kg/day) throughout organogenesis showed no evidence of teratogenicity up to the highest doses tested. In rats, reduced fetal weight and increased incidences of skeletal variations and/or delayed ossification were observed at the mid and high doses. The no-observed-effect dose for adverse effects on embryofetal development is 200 times the maximum recommended human dose (MRHD) of 3 mg/day on a mg/m ^2basis. No effects on embryofetal development were observed in rabbits; the highest dose tested is approximately 100 times the MRHD on a mg/m ^2basis.
Oral administration of eszopiclone (60, 120, or 180 mg/kg/day) to pregnant rats throughout the pregnancy and lactation resulted in increased post-implantation loss, decreased postnatal pup weights and survival, and increased pup startle response at all doses. The lowest dose tested is approximately 200 times the MRHD on a mg/m ^2basis. Eszopiclone had no effects on other developmental measures or reproductive function in the offspring.

8.2 Lactation

Risk Summary
There are no data on the presence of eszopiclone in either human or animal milk, the effects on the breastfed infant, or the effects on milk production. The developmental and health benefits of breastfeeding should be considered along with the mother’s clinical need for eszopiclone and any potential adverse effects on the breastfed infant from eszopiclone or from the underlying maternal condition.

8.4 Pediatric Use

Safety and effectiveness of eszopiclone tablets have not been established in pediatric patients.
Eszopiclone tablets failed to demonstrate efficacy in controlled clinical studies of pediatric patients with Attention-Deficit/Hyperactivity (ADHD) associated insomnia.
In a 12–week controlled study, 483 pediatric patients (aged 6 to17 years) with insomnia associated with ADHD (with 65% of the patients using concomitant ADHD treatments) were treated with oral tablets of eszopiclone (1, 2 or 3 mg tablets, n=323), or placebo (n=160). Eszopiclone did not significantly decrease latency to persistent sleep, compared to placebo, as measured by polysomnography after 12 weeks of treatment. Psychiatric and nervous system disorders comprised the most frequent treatment-emergent adverse reactions observed with eszopiclone versus placebo and included dysgeusia (9% vs.1%), dizziness (6% vs. 2%), hallucinations (2% vs. 0%) and suicidal ideation (0.3% vs. 0%). Nine patients on eszopiclone (3%) discontinued treatment due to an adverse reaction compared to 3 patients on placebo (2%).
In studies in which eszopiclone (2 to 300 mg/kg/day) was orally administered to young rats from weaning through sexual maturity, neurobehavioral impairment (altered auditory startle response) and reproductive toxicity (adverse effects on male reproductive organ weights and histopathology) were observed at doses ≥5 mg/kg/day. Delayed sexual maturation was noted in males and females at ≥10 mg/kg/day. The no-effect dose (2 mg/kg) was associated with plasma exposures (AUC) for eszopiclone and metabolite (S)-desmethylzopiclone [(S)-DMZ] approximately 2 times plasma exposures in humans at the MRHD in adults (3 mg/day).
When eszopiclone (doses from 1 to 50 mg/kg/day) was orally administered to young dogs from weaning through sexual maturity, neurotoxicity (convulsions) was observed at doses ≥ 5 mg/kg/day. Hepatotoxicity (elevated liver enzymes and hepatocellular vacuolation and degeneration) and reproductive toxicity (adverse effects on male reproductive organ weights and histopathology) were noted at dose ≥10 mg/kg/day. The no-effect dose (1 mg/kg) was associated with plasma exposures (AUC) to eszopiclone and (S)-DMZ approximately 3 and 2 times, respectively, plasma exposures in humans at the MRHD in adults.

8.5 Geriatric Use

A total of 287 subjects in double-blind, parallel-group, placebo-controlled clinical trials who received eszopiclone were 65 to 86 years of age. The overall pattern of adverse events for elderly subjects (median age = 71 years) in 2-week studies with nighttime dosing of 2 mg eszopiclone was not different from that seen in younger adults [see ]. Eszopiclone tablets 2 mg exhibited significant reduction in sleep latency and improvement in sleep maintenance in the elderly population. Compared with nonelderly adults, subjects 65 years and older had longer elimination and higher total exposure to eszopiclone. Therefore, dose reduction is recommended in elderly patients [see Error! Hyperlink reference not valid., Error! Hyperlink reference not valid.] .

8.6 Hepatic Impairment

No dose adjustment is necessary for patients with mild-to-moderate hepatic impairment. Exposure was increased in severely impaired patients compared with healthy volunteers. The dose of eszopiclone tablets should not exceed 2 mg in patients with severe hepatic impairment. Eszopiclone tablets should be used with caution in patients with hepatic impairment [see Error! Hyperlink reference not valid., Error! Hyperlink reference not valid.].

9 DRUG ABUSE AND DEPENDENCE

9.1 Controlled Substance

Eszopiclone tablet is a Schedule IV controlled substance under the Controlled Substances Act. Other substances under the same classification are benzodiazepines and the nonbenzodiazepine hypnotics zaleplon and zolpidem. While eszopiclone is a hypnotic agent with a chemical structure unrelated to benzodiazepines, it shares some of the pharmacologic properties of the benzodiazepines.

9.2 Abuse

Abuse and addiction are separate and distinct from physical dependence and tolerance. Abuse is characterized by misuse of the drug for nonmedical purposes, often in combination with other psychoactive substances. Physical dependence is a state of adaptation that is manifested by a specific withdrawal syndrome that can be produced by abrupt cessation, rapid dose reduction, decreasing blood level of the drug and/or administration of an antagonist. Tolerance is a state of adaptation in which exposure to a drug induces changes that result in a diminution of one or more of the drug’s effects over time. Tolerance may occur to both the desired and undesired effects of drugs and may develop at different rates for different effects.
Addiction is a primary, chronic, neurobiological disease with genetic, psychosocial, and environmental factors influencing its development and manifestations. It is characterized by behaviors that include one or more of the following: impaired control over drug use, compulsive use, continued use despite harm, and craving. Drug addiction is a treatable disease, utilizing a multidisciplinary approach, but relapse is common.
In a study of abuse liability conducted in individuals with known histories of benzodiazepine abuse, eszopiclone at doses of 6 and 12 mg produced euphoric effects similar to those of diazepam 20 mg. In this study, at doses 2-fold or greater than the maximum recommended doses, a dose-related increase in reports of amnesia and hallucinations was observed for both eszopiclone tablets and diazepam.

9.3 Dependence

The clinical trial experience with eszopiclone tablets revealed no evidence of a serious withdrawal syndrome. Nevertheless, the following adverse events included in DSM-IV criteria for uncomplicated sedative/hypnotic withdrawal were reported during clinical trials following placebo substitution occurring within 48 hours following the last eszopiclone tablets treatment: anxiety, abnormal dreams, nausea, and upset stomach. These reported adverse events occurred at an incidence of 2% or less. Use of benzodiazepines and similar agents may lead to physical and psychological dependence. The risk of abuse and dependence increases with the dose and duration of treatment and concomitant use of other psychoactive drugs. The risk is also greater for patients who have a history of alcohol or drug abuse or history of psychiatric disorders. These patients should be under careful surveillance when receiving eszopiclone tablets or any other hypnotic.

9.4 Tolerance

Some loss of efficacy to the hypnotic effect of benzodiazepines and benzodiazepine-like agents may develop after repeated use of these drugs for a few weeks.
No development of tolerance to any parameter of sleep measurement was observed over six months. Tolerance to the efficacy of eszopiclone tablets 3 mg was assessed by 4-week objective and 6-week subjective measurements of time to sleep onset and sleep maintenance for eszopiclone tablets in a placebo-controlled 44-day study, and by subjective assessments of time to sleep onset and wake time after sleep onset (WASO) in a placebo-controlled study for 6 months.

10 OVERDOSAGE

In clinical trials with eszopiclone, one case of overdose with up to 36 mg of eszopiclone was reported in which the subject fully recovered. Since commercial marketing began, spontaneous cases of eszopiclone overdoses up to 270 mg (90 times the maximum recommended dose of eszopiclone) have been reported, in which patients have recovered. Fatalities related to eszopiclone tablets overdoses were reported only in combination with other CNS drugs or alcohol.

10.1 Signs and Symptoms

Signs and symptoms of overdose effects of CNS depressants can be expected to present as exaggerations of the pharmacological effects noted in preclinical testing. Impairment of consciousness ranging from somnolence to coma has been described. Rare individual instances of fatal outcomes following overdose with racemic zopiclone have been reported in European postmarketing reports, most often associated with overdose with other CNS-depressant agents. Methemoglobinemia in association with overdoses of racemic zopiclone has been reported.

10.2 Recommended Treatment

General symptomatic and supportive measures should be used along with immediate gastric lavage where appropriate. Intravenous fluids should be administered as needed. Flumazenil may be useful. As in all cases of drug overdose, respiration, pulse, blood pressure, and other appropriate signs should be monitored and general supportive measures employed. Hypotension and CNS depression should be monitored and treated by appropriate medical intervention. Consider monitoring methemoglobin in the setting of high-dose overdosage. The value of dialysis in the treatment of overdosage has not been determined.
As with the management of all overdosage, the possibility of multiple drug ingestion should be considered. The physician may wish to consider contacting a poison control center for up-to-date information on the management of hypnotic drug product overdosage.

11 DESCRIPTION

Eszopiclone is a hypnotic agent/nonbenzodiazepine hypnotic agent that is a pyrrolopyrazine derivative of the cyclopyrrolone class. The chemical name of eszopiclone is (+)-4-Methyl-1-piperazinecarboxylic acid 6-(5-chloro-2-pyridinyl)-6,7-dihydro-7-oxo-5 Hpyrrolo[3,4- b]pyrazin-5-(S)-yl ester. Its molecular weight is 388.81, and its molecular formula is C 17H 17ClN 6O 3. Eszopiclone has a single chiral center with an (S)-configuration. It has the following chemical structure:

Eszopiclone USP is a white to slight yellowish powder. Eszopiclone USP is soluble in methylene chloride and dilute hydrochloric acid; practically insoluble in water and in alcohol.
Eszopiclone is formulated as film-coated tablets for oral administration. Eszopiclone tablets, USP contain 1 mg, 2 mg, or 3 mg eszopiclone USP and the following inactive ingredients: anhydrous dibasic calcium phosphate, croscarmellose sodium, colloidal silicon dioxide, hypromellose lactose monohydrate, magnesium stearate, microcrystalline cellulose, polyethylene glycol, titanium dioxide, and triacetin. In addition, both the 1 mg and 3 mg tablets contain FD&C Blue #2/indigo carmine aluminium lake.

12 CLINICAL PHARMACOLOGY

12.1 Mechanism of Action

The mechanism of action of eszopiclone as a hypnotic is unclear; however, its effect could be related to its interaction with GABA-receptor complexes at binding domains located close to or allosterically coupled to benzodiazepine receptors.

12.3 Pharmacokinetics

The pharmacokinetics of eszopiclone have been investigated in healthy subjects (adult and elderly) and in patients with hepatic disease or renal disease. In healthy subjects, the pharmacokinetic profile was examined after single doses of up to 7.5 mg and after once-daily administration of 1, 3, and 6 mg for 7 days. Eszopiclone is rapidly absorbed, with a time to peak concentration (t max)of approximately 1 hour and a terminal-phase elimination half-life (t 1/2) of approximately 6 hours. In healthy adults, eszopiclone tablets does not accumulate with once-daily administration, and its exposure is dose-proportional over the range of 1 to 6 mg.
Absorption and Distribution
Eszopiclone is rapidly absorbed following oral administration. Peak plasma concentrations are achieved within approximately 1 hour after oral administration. Eszopiclone is weakly bound to plasma protein (52 to 59%). The large free fraction suggests that eszopiclone disposition should not be affected by drug-drug interactions caused by protein binding. The blood-to-plasma ratio for eszopiclone is less than one, indicating no selective uptake by red blood cells.
Metabolism
Following oral administration, eszopiclone is extensively metabolized by oxidation and demethylation. The primary plasma metabolites are (S)-zopiclone-N-oxide and (S)-N-desmethyl zopiclone; the latter compound binds to GABA receptors with substantially lower potency than eszopiclone, and the former compound shows no significant binding to this receptor. In vitrostudies have shown that CYP3A4 and CYP2E1 enzymes are involved in the metabolism of eszopiclone. Eszopiclone did not show any inhibitory potential on CYP450 1A2, 2A6, 2C9, 2C19, 2D6, 2E1, and 3A4 in cryopreserved human hepatocytes.
Elimination
After oral administration, eszopiclone is eliminated with a mean t 1/2of approximately 6 hours. Up to 75% of an oral dose of racemic zopiclone is excreted in the urine, primarily as metabolites. A similar excretion profile would be expected for eszopiclone, the S-isomer of racemic zopiclone. Less than 10% of the orally administered eszopiclone dose is excreted in the urine as parent drug.
Effect of Food
In healthy adults, administration of a 3 mg dose of eszopiclone after a high-fat meal resulted in no change in AUC, a reduction in mean C maxof 21%, and delayed t maxby approximately 1 hour.
The half-life remained unchanged, approximately 6 hours. The effects of eszopiclone tablets on sleep onset may be reduced if it is taken with or immediately after a high-fat/heavy meal.
Specific Populations
Age
Compared with nonelderly adults, subjects 65 years and older had an increase of 41% in total exposure (AUC) and a slightly prolonged elimination of eszopiclone (t 1/2approximately 9 hours). C maxwas unchanged. Therefore, in elderly patients the dose should not exceed 2 mg.
Gender
The pharmacokinetics of eszopiclone in men and women are similar.
Race
In an analysis of data on all subjects participating in Phase 1 studies of eszopiclone, the pharmacokinetics for all races studied appeared similar.
Hepatic Impairment
Pharmacokinetics of a 2 mg eszopiclone dose were assessed in 16 healthy volunteers and in 8 subjects with mild, moderate, and severe liver disease. Exposure was increased 2-fold in severely impaired patients compared with the healthy volunteers. C maxand t maxwere unchanged. No dose adjustment is necessary for patients with mild-to-moderate hepatic impairment. Dose reduction is recommended for patients with severe hepatic impairment. Eszopiclone tablets should be used with caution in patients with hepatic impairment [see Error! Hyperlink reference not valid.].
Renal Impairment
The pharmacokinetics of eszopiclone were studied in 24 patients with mild, moderate, or severe renal impairment. AUC and C maxwere similar in the patients compared with demographically matched healthy control subjects. No dose adjustment is necessary in patients with renal impairment, since less than 10% of the orally administered eszopiclone dose is excreted in the urine as parent drug.
Drug Interactions
Eszopiclone is metabolized by CYP3A4 and CYP2E1 via demethylation and oxidation. There were no pharmacokinetic or pharmacodynamic interactions between eszopiclone and paroxetine. When eszopiclone was coadministered with olanzapine, no pharmacokinetic interaction was detected in levels of eszopiclone or olanzapine, but a pharmacodynamic interaction was seen on a measure of psychomotor function. Eszopiclone and lorazepam decreased each other’s C maxby 22%. Coadministration of eszopiclone 3 mg to subjects receiving ketoconazole, a potent inhibitor of CYP3A4, 400 mg daily for 5 days, resulted in a 2.2-fold increase in exposure to eszopiclone. C maxand t 1/2were increased 1.4-fold and 1.3-fold, respectively. Eszopiclone tablets would not be expected to alter the clearance of drugs metabolized by common CYP450 enzymes [see Error! Hyperlink reference not valid., Error! Hyperlink reference not valid.].
Paroxetine:Coadministration of single dose of eszopiclone and paroxetine produced no pharmacokinetic or pharmacodynamic interaction. The lack of a drug interaction following single-dose administration does not predict the complete absence of a pharmacodynamic effect following chronic administration.
Lorazepam:Coadministration of single doses of eszopiclone and lorazepam did not have clinically relevant effects on the pharmacodynamics or pharmacokinetics of either drug. The lack of a drug interaction following single-dose administration does not predict the complete absence of a pharmacodynamic effect following chronic administration.
Drugs with a Narrow Therapeutic Index
Digoxin:A single dose of eszopiclone 3 mg did not affect the pharmacokinetics of digoxin measured at steady state following dosing of 0.5 mg twice daily for one day and 0.25 mg daily for the next 6 days.
Warfarin:Eszopiclone 3 mg administered daily for 5 days did not affect the pharmacokinetics of (R)- or (S)-warfarin, nor were there any changes in the pharmacodynamic profile (prothrombin time) following a single 25 mg oral dose of warfarin.
Drugs Highly Bound to Plasma Protein
Eszopiclone is not highly bound to plasma proteins (52 to 59% bound); therefore, the disposition of eszopiclone is not expected to be sensitive to alterations in protein binding. Administration of eszopiclone 3 mg to a patient taking another drug that is highly protein-bound would not be expected to cause an alteration in the free concentration of either drug.

13 NONCLINICAL TOXICOLOGY

13.1 Carcinogenesis & Mutagenesis & Impairment Of Fertility

Carcinogenesis
In a carcinogenicity study in rats, oral administration of eszopiclone for 97 (males) or 104 (females) weeks resulted in no increases in tumors; plasma levels (AUC) of eszopiclone at the highest dose tested (16 mg/kg/day) are approximately 80 (females) and 20 (males) times those in humans at the MRHD of 3 mg/day. However, in a 2-year carcinogenicity study in rats, oral administration of racemic zopiclone (1, 10, or 100 mg/kg/day) resulted in increases in mammary gland adenocarcinomas (females) and thyroid gland follicular cell adenomas and carcinomas (males) at the highest dose tested. Plasma levels of eszopiclone at this dose are approximately 150 (females) and 70 (males) times those in humans at the MRHD of eszopiclone. The mechanism for the increase in mammary adenocarcinomas is unknown. The increase in thyroid tumors is thought to be due to increased levels of TSH secondary to increased metabolism of circulating thyroid hormones, a mechanism not considered relevant to humans.
In a 2-year carcinogenicity study in mice, oral administration of racemic zopiclone (1, 10, or 100 mg/kg/day) produced increases in pulmonary carcinomas and carcinomas plus adenomas (females) and skin fibromas and sarcomas (males) at the highest dose tested. The skin tumors were due to skin lesions induced by aggressive behavior, a mechanism not relevant to humans. A carcinogenicity study of eszopiclone was conducted in mice at oral doses up to 100 mg/kg/day. Although this study did not reach a maximum tolerated dose, and was thus inadequate for overall assessment of carcinogenic potential, no increases in either pulmonary or skin tumors were seen at doses producing plasma levels of eszopiclone approximately 90 times those in humans at the MRHD of eszopiclone (and 12 times the exposure in the racemate study).
Eszopiclone did not increase tumors in a p53 transgenic mouse bioassay at oral doses up to 300 mg/kg/day.
Mutagenesis
Eszopiclone was clastogenic in in vitro(mouse lymphoma and chromosomal aberration) assays in mammalian cells. Eszopiclone was negative in the in vitrobacterial gene mutation (Ames) assay and in an in vivomicronucleus assay.
(S)-N-desmethyl zopiclone, a metabolite of eszopiclone, was positive in in vitrochromosomal aberration assays in mammalian cells. (S)-N-desmethyl zopiclone was negative in the in vitrobacterial gene mutation (Ames) assay and in an in vivochromosomal aberration and micronucleus assay.
Impairment of Fertility
Oral administration of eszopiclone to rats prior to and during mating, and continuing in females to day 7 of gestation (doses up to 45 mg/kg/day to males and females or up to 180 mg/kg/day to females only) resulted in decreased fertility, with no pregnancy at the highest dose tested when both males and females were treated. In females, there was an increase in abnormal estrus cycles at the highest dose tested. In males, decreases in sperm number and motility and increases in morphologically abnormal sperm were observed at the mid and high doses. The no-effect dose for adverse effects on fertility (5 mg/kg/day) is 16 times the MRHD on a mg/m ^2basis.

14 CLINICAL STUDIES

The effect of eszopiclone tablets on reducing sleep latency and improving sleep maintenance was established in studies with 2100 subjects (ages 18 to 86) with chronic and transient insomnia in six placebo-controlled trials of up to 6 months’ duration. Two of these trials were in elderly patients (n=523). Overall, at the recommended adult dose (2 to 3 mg) and elderly dose (1 to 2 mg), eszopiclone tablets significantly decreased sleep latency and improved measures of sleep maintenance (objectively measured as wake time after sleep onset [WASO] and subjectively measured as total sleep time).

14.1 Transient Insomnia

Healthy adults were evaluated in a model of transient insomnia (n=436) in a sleep laboratory in a double-blind, parallel-group, single-night trial comparing two doses of eszopiclone and placebo. Eszopiclone tablets 3 mg was superior to placebo on measures of sleep latency and sleep maintenance, including polysomnographic (PSG) parameters of latency to persistent sleep (LPS) and WASO.

14.2 Chronic Insomnia (Adults and Elderly)

The effectiveness of eszopiclone tablets was established in five controlled studies in chronic insomnia. Three controlled studies were in adult subjects, and two controlled studies were in elderly subjects with chronic insomnia.
Adults
In the first study, adults with chronic insomnia (n=308) were evaluated in a double-blind, parallel-group trial of 6 weeks’ duration comparing eszopiclone tablets 2 mg and 3 mg with placebo. Objective endpoints were measured for 4 weeks. Both 2 mg and 3 mg were superior to placebo on LPS at 4 weeks. The 3 mg dose was superior to placebo on WASO.
In the second study, adults with chronic insomnia (n=788) were evaluated using subjective measures in a double-blind, parallel-group trial comparing the safety and efficacy of eszopiclone tablets 3 mg with placebo administered nightly for 6 months. Eszopiclone tablets was superior to placebo on subjective measures of sleep latency, total sleep time, and WASO.
In addition, a 6-period crossover PSG study evaluating eszopiclone doses of 1 to 3 mg, each given over a 2-day period, demonstrated effectiveness of all doses on LPS, and of 3 mg on WASO. In this trial, the response was dose related.
Elderly
Elderly subjects (ages 65 to 86 years) with chronic insomnia were evaluated in two double-blind, parallel-group trials of 2 weeks duration. One study (n=231) compared the effects of eszopiclone tablets with placebo on subjective outcome measures, and the other (n=292) on objective and subjective outcome measures. The first study compared 1 mg and 2 mg of eszopiclone tablets with placebo, while the second study compared 2 mg of eszopiclone tablets with placebo. All doses were superior to placebo on measures of sleep latency. In both studies, 2 mg of eszopiclone tablets was superior to placebo on measures of sleep maintenance.

14.3 Studies Pertinent to Safety Concerns for Sedative Hypnotic Drugs

Next-Day Residual Effects
In a double-blind study of 91 healthy adults age 25-to 40 years, the effects of eszopiclone tablets 3 mg on psychomotor function were assessed between 7.5 and 11.5 hours the morning after dosing. Measures included tests of psychomotor coordination that are correlated with ability to maintain a motor vehicle in the driving lane, tests of working memory, and subjective perception of sedation and coordination. Compared with placebo, eszopiclone tablets 3 mg was associated with next-morning psychomotor and memory impairment that was most severe at 7.5 hours, but still present and potentially clinically meaningful at 11.5 hours. Subjective perception of sedation and coordination from eszopiclone tablets 3 mg was not consistently different from placebo, even though subjects were objectively impaired.
In a 6-month double-blind, placebo-controlled trial of nightly administered eszopiclone tablets 3 mg, memory impairment was reported by 1.3% (8/593) of subjects treated with eszopiclone tablets 3 mg compared to 0% (0/195) of subjects treated with placebo. In a 6-week adult study of nightly administered eszopiclone tablets confusion was reported by 3.0% of patients treated with eszopiclone tablets 3 mg, compared to 0% of subjects treated with placebo. In the same study, memory impairment was reported by 1% of patients treated with either 2 mg or 3 mg eszopiclone tablets, compared to 0% treated with placebo.
In a 2-week study of 264 elderly insomniacs, 1.5% of patients treated with eszopiclone tablets 2 mg reported memory impairment compared to 0% treated with placebo. In another 2-week study of 231 elderly insomniacs, 2.5% of patients treated with eszopiclone tablets 2 mg reported confusion compared to 0% treated with placebo.
Withdrawal-Emergent Anxiety and Insomnia
During nightly use for an extended period, pharmacodynamic tolerance or adaptation has been observed with other hypnotics. If a drug has a short elimination half-life, it is possible that a relative deficiency of the drug or its active metabolites (i.e., in relationship to the receptor site) may occur at some point in the interval between each night’s use. This is believed to be responsible for two clinical findings reported to occur after several weeks of nightly use of other rapidly eliminated hypnotics: increased wakefulness during the last quarter of the night and the appearance of increased signs of daytime anxiety.
In a 6-month double-blind, placebo-controlled study of nightly administration of eszopiclone tablets 3 mg, rates of anxiety reported as an adverse event were 2.1% in the placebo arm and 3.7% in the eszopiclone tablets arm. In a 6-week adult study of nightly administration, anxiety was reported as an adverse event in 0%, 2.9%, and 1.0% of the placebo, 2 mg, and 3 mg treatment arms, respectively. In this study, single-blind placebo was administered on nights 45 and 46, the first and second days of withdrawal from study drug. New adverse events were recorded during the withdrawal period, beginning with day 45, up to 14 days after discontinuation. During this withdrawal period, 105 subjects previously taking nightly eszopiclone tablets 3 mg for 44 nights spontaneously reported anxiety (1%), abnormal dreams (1.9%), hyperesthesia (1%), and neurosis (1%), while none of 99 subjects previously taking placebo reported any of these adverse events during the withdrawal period.
Rebound insomnia, defined as a dose-dependent temporary worsening in sleep parameters (latency, sleep efficiency, and number of awakenings) compared with baseline following discontinuation of treatment, is observed with short- and intermediate-acting hypnotics. Rebound insomnia following discontinuation of eszopiclone tablets relative to placebo and baseline was examined objectively in a 6-week adult study on the first 2 nights of discontinuation (nights 45 and 46) following 44 nights of active treatment with 2 mg or 3 mg. In the eszopiclone tablets 2 mg group, compared with baseline, there was a significant increase in WASO and a decrease in sleep efficiency, both occurring only on the first night after discontinuation of treatment. No changes from baseline were noted in the eszopiclone tablets 3 mg group on the first night after discontinuation, and there was a significant improvement in LPS and sleep efficiency compared with baseline following the second night of discontinuation. Comparisons of changes from baseline between eszopiclone tablets and placebo were also performed. On the first night after discontinuation of eszopiclone tablets 2 mg, LPS and WASO were significantly increased and sleep efficiency was reduced; there were no significant differences on the second night. On the first night following discontinuation of eszopiclone tablets 3 mg, sleep efficiency was significantly reduced. No other differences from placebo were noted in any other sleep parameter on either the first or second night following discontinuation. For both doses, the discontinuation-emergent effect was mild, had the characteristics of the return of the symptoms of chronic insomnia, and appeared to resolve by the second night after eszopiclone tablets discontinuation.

16 HOW SUPPLIED/STORAGE AND HANDLING

NDC 82804-159-90
Eszopiclone tablets USP, 1 mg are light blue, round, biconvex, film-coated tablets debossed with ‘H’ on one side and ‘E14’ on the other side.
Bottles of 30 tablets NDC 82804-159-30

Bottles of 60 tablets NDC 82804-159-60

Bottles of 90 tablets NDC 82804-159-90

Store at 20° to 25° C (68° to 77° F) [see USP Controlled Room Temperature].

17 PATIENT COUNSELING INFORMATION

See FDA-approved patient labeling (Error! Hyperlink reference not valid.).
Inform patients and their families about the benefits and risks of treatment with eszopiclone tablets. Inform patients of the availability of a Medication Guide and instruct them to read the Medication Guide prior to initiating treatment with eszopiclone tablets and with each prescription refill. Review the eszopiclone tablets Medication Guide with every patient prior to initiation of treatment. Instruct patients or caregivers that eszopiclone tablets should be taken only as prescribed.
Complex Sleep Behaviors
Instruct patients and their families that ESZOPICLONE TABLETS may cause complex sleep behaviors, including sleep-walking, sleep-driving, preparing and eating food, making phone calls, or having sex while not being fully awake. Serious injuries and death have occurred during complex sleep behavior episodes. Tell patients to discontinue ESZOPICLONE TABLETS and notify their healthcare provider immediately if they develop any of these symptoms [see Boxed Warning, Error! Hyperlink reference not valid.].
CNS Depressant Effects and Next-Day Impairment
Tell patients that eszopiclone tablets can cause next-day impairment even when used as prescribed, and that this risk is increased if dosing instructions are not carefully followed. Caution patients taking the 3 mg dose against driving and other activities requiring complete mental alertness the day after use. Inform patients that impairment can be present despite feeling fully awake. Advise patients that increased drowsiness and decreased consciousness may increase the risk of falls in some patients [see Error! Hyperlink reference not valid.].
Severe Anaphylactic and Anaphylactoid Reactions
Inform patients that severe anaphylactic and anaphylactoid reactions have occurred with eszopiclone. Describe the signs/symptoms of these reactions and advise patients to seek medical attention immediately if any of them occur [see Error! Hyperlink reference not valid.].
Suicide
Tell patients to immediately report any suicidal thoughts.
Alcohol and Other Drugs
Ask patients about alcohol consumption, medicines they are taking, and drugs they may be taking without a prescription. Advise patients not to use eszopiclone tablets if they drank alcohol that evening or before bed.
Tolerance, Abuse, and Dependence
Tell patients not to increase the dose of eszopiclone tablets on their own, and to inform you if they believe the drug "does not work.”
Administration Instructions
Patients should be counseled to take eszopiclone tablets right before they get into bed and only when they are able to stay in bed a full night (7 to 8 hours) before being active again. Eszopiclone tablets should not be taken with or immediately after a meal. Advise patients NOT to take eszopiclone tablets if they drank alcohol that evening.

Manufactured for:
Camber Pharmaceuticals, Inc.
Piscataway, NJ 08854
By: Annora Pharma Pvt. Ltd.
Sangareddy - 502313, Telangana, India.

Repackaged by:
Proficient Rx LP
Thousand Oaks, CA 91320

Revised: 01/2023

MEDICATION GUIDE

Eszopiclone Tablets, USP C-IV
(ess-ZOP-ih-klone)

Read the Medication Guide that comes with eszopiclone tablets before you start taking it and each time you get a refill. There may be new information. This Medication Guide does not take the place of talking to your doctor about your medical condition or treatment.

What is the most important information I should know about eszopiclone tablets?
• Do not take more eszopiclone tablets than prescribed.
• Do not take eszopiclone tablets unless you are able to stay in bed a full night (7 to 8 hours) before you must be active again.
• Take eszopiclone tablets right before you get in bed, not sooner.
Eszopiclone tablets may cause serious side effects, including:
Complex sleep behaviors that have caused serious injury and death.After taking eszopiclone tablets, you may get up out of bed while not being fully awake and do an activity that you do not know you are doing (complex sleep behaviors). The next morning, you may not remember that you did anything during the night. These activities may occur with eszopiclone tablets whether or not you drink alcohol or take other medicines that make you sleepy.
Reported activities and behaviors include:
• doing activities when you are asleep like:
o making and eating food
o talking on the phone
o having sex
o driving a car (“sleep-driving”)
o sleep walking
Stop taking eszopiclone tablets and call your healthcare provider right away if you find out that you have done any of the above activities after taking eszopiclone tablets.
The morning after you take eszopiclone tablets your ability to drive safely and think clearly may be decreased. You also may experience sleepiness during the day.
Do not take eszopiclone tablets if you:
• have ever experienced a complex sleep behavior (such as driving a car, making and eating food, talking on the phone or having sex while not fully awake) after taking eszopiclone tablets.
• drank alcohol that evening or before bed
• take other medicines that can make you sleepy. Talk to your doctor about all of your medicines. Your doctor will tell you if you can take eszopiclone tablets with your other medicines.
• cannot get a full night’s sleep
WHAT ARE ESZOPICLONE TABLETS?
Eszopiclone tablets are a sedative-hypnotic (sleep) medicine. Eszopiclone tablets are used in adults for the treatment of a sleep problem called insomnia. Symptoms of insomnia include:
• trouble falling asleep
• waking up often during the night
Eszopiclone tablets are not for children.

Eszopiclone tablets are a federally controlled substance (C-IV) because it can be abused or lead to dependence. Keep eszopiclone tablets in a safe place to prevent misuse and abuse. Selling or giving away eszopiclone tablets may harm others, and is against the law. Tell your doctor if you have ever abused or been dependent on alcohol, prescription medicines or street drugs.

Who should not take eszopiclone tablets?
• Do not take eszopiclone tablets if you have ever had a complex sleep behavior happen after taking eszopiclone tablets.
• Do not take eszopiclone tablets if you are allergic to anything in it. See the end of this Medication Guide for a complete list of ingredients in eszopiclone tablets.
Eszopiclone tablets may not be right for you. Before starting eszopiclone tablets, tell your doctor about all of your health conditions, including if you:
• have a history of depression, mental illness, or suicidal thoughts
• have a history of drug or alcohol abuse or addiction
• have liver disease
• are pregnant, planning to become pregnant, or breastfeeding
Tell your doctor about all of the medicines you take including prescription and nonprescription medicines, vitamins and herbal supplements. Medicines can interact with each other, sometimes causing serious side effects. Do not take eszopiclone tablets with other medicines that can make you sleepy.
Know the medicines you take. Keep a list of your medicines with you to show your doctor and pharmacist each time you get a new medicine.
How should I take eszopiclone tablets?
• Take eszopiclone tablets exactly as prescribed. Do not take more eszopiclone tablets than prescribed for you.
• Take eszopiclone tablets right before you get into bed.
• Do not take eszopiclone tablets with or right after a meal.
• Do not take eszopiclone tablets unless you are able to get a full night’s sleep before you must be active again.
• Call your doctor if your insomnia worsens or is not better within 7 to 10 days. This may mean that there is another condition causing your sleep problems.
• If you take too much eszopiclone tablets or overdose, call your doctor or poison control center right away, or get emergency treatment.
What are the possible side effects of eszopiclone tablets?
Possible serious side effects of eszopiclone tablets include:
• getting out of bed while not being fully awake and doing an activity that you do not know you are doing.(See “What is the most important information I should know about eszopiclone tablets?”)
• abnormal thoughts and behavior.Symptoms include more outgoing or aggressive behavior than normal, confusion, agitation, acting strangely, hallucinations, worsening of depression, and suicidal thoughts or actions.
• memory loss
• anxiety
• severe allergic reactions. Symptoms include swelling of the tongue or throat, trouble breathing, and nausea and vomiting. Get emergency medical help if you get these symptoms after taking eszopiclone tablets.
Call your doctor right away if you have any of the above side effects or any other side effects that worry you while using eszopiclone tablets.
The most common side effects of eszopiclone tablets are:
• unpleasant taste in mouth, dry mouth
• drowsiness
• dizziness
• headache
• symptoms of the common cold
• You may still feel drowsy the next day after taking eszopiclone tablets. Do not drive or do other dangerous activities after taking eszopiclone tablets until you feel fully awake.
These are not all the side effects of eszopiclone tablets. Ask your doctor or pharmacist for more information. Call your doctor for medical advice about side effects. You may report side effects to FDA at 1-800-FDA-1088.
How should I store eszopiclone tablets?
• Store eszopiclone tablets at 68°F to 77° F (20°C to 25° C) .
• Do not use eszopiclone tablets after the expiration date.
• Keep eszopiclone tablets and all medicines out of reach of children.
General Information about eszopiclone tablets
• Medicines are sometimes prescribed for purposes other than those listed in a Medication Guide.
• Do not use eszopiclone tablets for a condition for which it was not prescribed.
• Do not share eszopiclone tablets with other people, even if you think they have the same symptoms that you have. It may harm them and is against the law.
This Medication Guide summarizes the most important information about eszopiclone tablets. If you would like more information, talk with your doctor. You can ask your doctor or pharmacist for information about eszopiclone tablets that is written for healthcare professionals.
• For more information, call 1-866-495-1995.
What are the ingredients in eszopiclone tablets?
Active Ingredient: eszopiclone USP
Inactive Ingredients:calcium phosphate, colloidal silicon dioxide, croscarmellose sodium, hypromellose, lactose, magnesium stearate, microcrystalline cellulose, polyethylene glycol, titanium dioxide, and triacetin. In addition, both the 1 mg and 3 mg tablets contain FD&C Blue #2/indigo carmine aluminium lake.
This Medication Guide has been approved by the U.S. Food and Drug Administration.
Medication Guide available at http://camberpharma.com/medication-guides

Manufactured for:
Camber Pharmaceuticals, Inc.
Piscataway, NJ 08854

By: Annora Pharma Pvt. Ltd.
Sangareddy - 502313, Telangana, India.

Repackaged by:
Proficient Rx LP
Thousand Oaks, CA 91320

Revised: 01/2023

PACKAGE LABEL.PRINCIPAL DISPLAY PANEL

1 mg-90's count container label